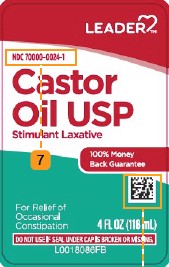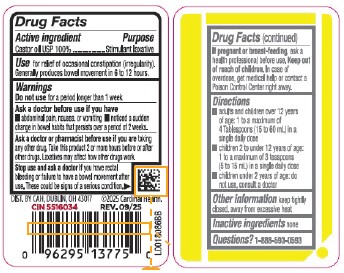 DRUG LABEL: Leader Castor Oil
NDC: 70000-0024 | Form: OIL
Manufacturer: Cardinal Health, 110 dba Leader
Category: otc | Type: HUMAN OTC DRUG LABEL
Date: 20260129

ACTIVE INGREDIENTS: CASTOR OIL 1 g/1 mL

Leader 078.000/078AA
Castor Oil

Active ingredient

Castor oil USP 100%

Purpose

Stimulant Laxative

Use

For relief of occasional constipation (irregularity). Generally produces bowel movement in 6 to 12 hours.

Warnings

for this product

Do not use

for a period longer than 1 week

Ask a doctor before use if you have

- abdominal pain, nausea, or vomiting
- noticed a sudden change in bowel habits that persists over a period of 2 weeks

Ask a doctor or pharmacist before use if you are

taking any other drug. Take this product 2 or more hours before or after other drugs. Laxatives may affect how other drugs work.

Stop use and ask a doctor

if you have rectal bleeding or failure to have a bowel movement after use. These could be signs of a serious condition.

If pregnant or breast-feeding,

ask a health professional before use.

Keep out of reach of children.

In case of overdose, get medical help or contact a Poison Control Center right away.

Directions

- Adults and children over 12 years of age: 1 to a maximum of 4 tablespoons (15 to 60 mL) in a single daily dose
- Children 2 to under 12 years of age: 1 to a maximum of 3 teaspoons (5 to 15 mL) in a single daily dose
- Children under 2 years of age: do not use, consult a doctor

INACTIVE INGREDIENT

none

Other information

Keep tightly closed, away from excessive heat.

Questions?

1-888-593-0593

Adverse reactions

Dist. by CAH, Dublin, OH 43017

©2025 Cardinal Health

CIN 5516034 REV. 09/25

principal display panel

LEADER ™

NDC 70000-0024-1

Castor Oil USP

Stimulant Laxative

100% Money Back Guarantee

For the Relief of Occasional Constipation

4 FL OZ (118 mL)

DO NOT USE IF SEAL UNDER CAP IS BROKEN OR MISSING.